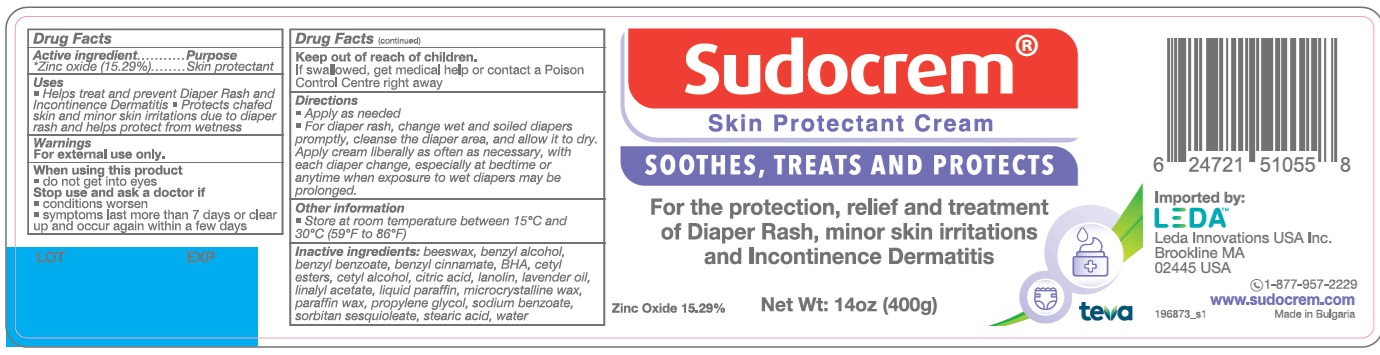 DRUG LABEL: SUDOCREM SKIN PROTECTANT
NDC: 84589-002 | Form: CREAM
Manufacturer: LEDA INNOVATIONS USA, INC.
Category: otc | Type: HUMAN OTC DRUG LABEL
Date: 20240829

ACTIVE INGREDIENTS: ZINC OXIDE 152.9 mg/1 g
INACTIVE INGREDIENTS: WATER; LANOLIN; LINALYL ACETATE; BENZYL CINNAMATE; BENZYL BENZOATE; SODIUM BENZOATE; MICROCRYSTALLINE WAX; PARAFFIN; PROPYLENE GLYCOL; BUTYLATED HYDROXYANISOLE; YELLOW WAX; BENZYL ALCOHOL; LAVENDER OIL; SORBITAN SESQUIOLEATE; CITRIC ACID MONOHYDRATE; STEARIC ACID; CETYL ALCOHOL; CETYL ESTERS WAX

SUDOCREM SKIN PROTECTANT CREAM

Active ingredient

Zinc oxide (15.29%)

Purpose

Skin protectant

Uses

- Helps treat and prevent Diaper Rash and Incontinence Dermatitis
- Protects chafed skin and minor skin irritations due to diaper rash and helps protect from wetness

Warnings

For external use only.

When using this product

- do not get into eyes

Stop use and ask a doctor if

- conditions worsens
- symptoms last more than 7 days or clear up and occur again within a few days

Keep out of reach of children.

If swallowed, get medical help or contact a Poison Control Center right away

Directions

- Apply as needed
- For diaper rash, change wet and soiled diapers promptly, cleanse the diaper area, and allow it to dry. Apply cream liberally as often as necessary, with each diaper change, especially at bedtime or anytime when exposure to wet diapers may be prolonged.

Other information

- Store at room temperature between 15C and 30C (59F to 86F)
- Do not use if safety seal is broken or missing

Inactive ingredients

beeswax, benzyl alcohol, benzyl benzoate, benzyl cinnamate, BHA, cetyl esters, cetyl alcohol, citric acid, lanolin, lavender oil, linalyl acetate, liquid paraffin, microcrystalline wax, paraffin wax, propylene glycol, sodium benzoate, sorbitan sesquioleate, stearic acid, water